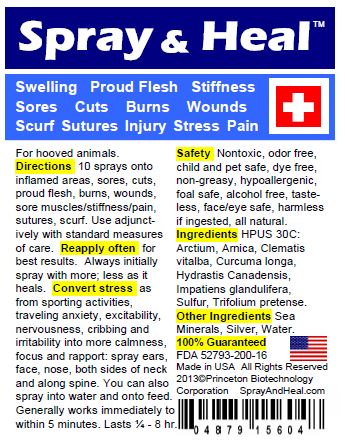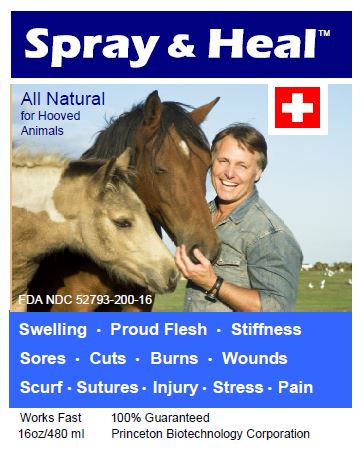 DRUG LABEL: Spray and Heal 
NDC: 52793-200 | Form: SPRAY
Manufacturer: PRINCETON BIOTECHNOLOGY CORPORATION
Category: animal | Type: OTC ANIMAL DRUG LABEL
Date: 20130104

ACTIVE INGREDIENTS: Arctium Lappa Root 30 [hp_C]/1 mL; Arnica Montana Flower 30 [hp_C]/1 mL; Clematis Vitalba Leaf 30 [hp_C]/1 mL; Turmeric 30 [hp_C]/1 mL; Goldenseal 30 [hp_C]/1 mL; Impatiens Glandulifera Flower 30 [hp_C]/1 mL; Sulfur 30 [hp_C]/1 mL; Trifolium Pratense Flower 30 [hp_C]/1 mL
INACTIVE INGREDIENTS: Silver; Water

Spray & Heal™

Active Ingredients

HPUS 30C: Arctium, Arnica, Clematis vitalba, Curcuma longa, Hydrastis Canadensis, Impatiens glandulifera, Sulfur, Trifolium pratense.

Purpose

For hooved animals.

- Swelling
- Proud Flesh
- Stiffness
- Sores
- Cuts
- Burns
- Wounds
- Scurf
- Sutures
- Injury
- Stress
- Pain

Directions

5-10 sprays onto inflamed areas, sores, cuts, proud flesh, burns, wounds, sore muscles/stiffness/pain, sutures, scurf.

Use adjunctively with standard measures of care.

Reapply often for best results.

Always initially spray with more; less as it heals.

Convert stress as from sporting activities, traveling anxiety, excitability, nervousness, cribbing and irritability into more calmness, focus and rapport: spray ears, face, nose, both sides of neck and along spine.

You can also spray into water and onto feed.

Generally works immediately to within 5 minutes. Lasts ¼ - 8 hr.

Safety

Nontoxic, odor free, child and pet safe, dye free, non-greasy, hypoallergenic, foal safe, alcohol free, tasteless, face/eye safe, harmless if ingested, all natural.

Other Ingredients

Sea Minerals, Silver, Water.

Questions?

SprayAndHeal.com

Principal Display Panels

Spray & Heal™
All Natural
for Hooved Animals
FDA NDC 52793-200-16
Swelling ● Proud Flesh ● Stiffness ● Sores ● Cuts ● Burns ● Wounds ● Scurf ● Sutures ● Injury ● Stress ● Pain
Works Fast
100% Guaranteed
16oz/480 ml
Princeton Biotechnology Corporation

For hooved animals.
Directions 5-10 sprays onto inflamed areas, sores, cuts, proud flesh, burns, wounds, sore muscles/stiffness/pain, sutures. Use adjunctively with standard measures of care.
Reapply often for best results. Always initially spray with more; less as it heals.
Convert stress as from sporting activities, traveling anxiety, excitability, nervousness, cribbing and irritability into more calmness, focus and rapport: spray ears, face, nose, both sides of neck and along spine. You can also spray into water and onto feed. Generally works immediately to within 5 minutes. Lasts ¼ - 8 hr.
Safety Nontoxic, odor free, child and pet safe, dye free, non-greasy, hypoallergenic, foal safe, alcohol free, tasteless, face/eye safe, harmless if ingested, all natural.
Ingredients HPUS 30C: Arctium, Arnica, Clematis vitalba, Curcuma longa, Hydrastis Canadensis, Impatiens glandulifera, Sulfur, Trifolium pratense.
Other Ingredients Sea Minerals, Silver, Water.
100% Guaranteed
FDA 52793-200-16
Made in USA
All Rights Reserved 2013
©Princeton Biotechnology Corporation
SprayAndHeal.com